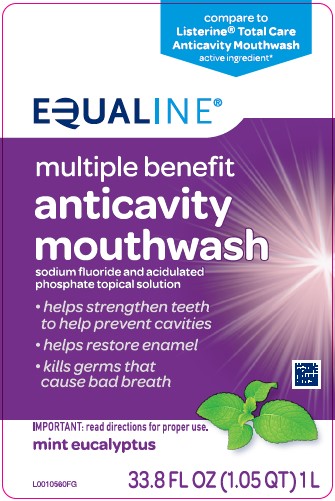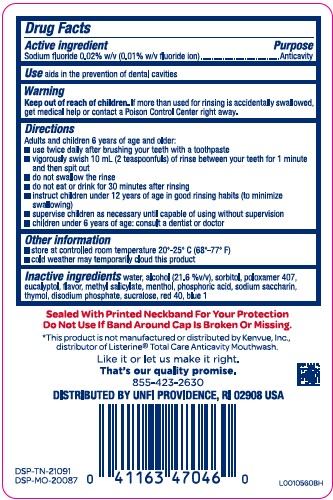 DRUG LABEL: Anticavity
NDC: 41163-043 | Form: MOUTHWASH
Manufacturer: United Natural Foods, Inc. dba UNFI
Category: otc | Type: HUMAN OTC DRUG LABEL
Date: 20260216

ACTIVE INGREDIENTS: SODIUM FLUORIDE 0.1 mg/1 mL
INACTIVE INGREDIENTS: WATER; ALCOHOL; SORBITOL; POLOXAMER 407; EUCALYPTOL; METHYL SALICYLATE; MENTHOL; PHOSPHORIC ACID; SACCHARIN SODIUM; THYMOL; SODIUM PHOSPHATE, DIBASIC, ANHYDROUS; SUCRALOSE; FD&C RED NO. 40; FD&C BLUE NO. 1

Equaline 163.005/163AG
Anticavity Fluoride Rinse Mint

Active ingredient

Sodium fluoride 0.02% (0.01% w/v fluoride ion)

Purpose

Anticavity

Use

aids in the prevention of dental cavities

Warnings

for this product

Keep out of reach of children.

If more than used for rinsing is accidentally swallowed, get medical help or contact a Poison Control Center right away.

Directions

Adults and children 6 years of age and older:

- use twice daily after brushing your teeth with a toothpaste
- vigorously swish 10 mL (2 teaspoonfuls) of rinse between your teeth for 1 minute then spit out
- do not swallow the rinse
- do not eat or drink for 30 minutes after rinsing
- instruct children under 12 years of age in good rinsing habits (to minimize swallowing)
- supervise children as necessary until capable of using without supervision
- children under 6 years of age: consult a dentist or doctor

Other information

- store at controlled room temperature 20°-25° C to (68°-77°F)
- cold weather may temporarily cloud this product

Inactive ingredients

water, alcohol (21.6 %v/v), sorbitol, poloxamer 407, eucalyptol, flavor, methyl salicylate, menthol, phosphoric acid, sodium saccharin, thymol, disodium phosphate, sucralose, red 40, blue 1

Tamper Evident Statement

Sealed With Printed Neckband For Your Protection

Do Not Use If Band Around Cap Is Broken Or Missing.

Disclaimer

*This product is not manufactured or distributed by Kenvue, Inc, distributor of Listerine® Total Care Anticavity Mouthwash.

Adverse Reaction

Like it or let us make it right.

That's our quality promise.

855-423-2360

DISTRIBUTED BY UNFI PROVIDENCE, RI 02908 USA

DSP-TN-21091

DSP-MO-20087

Principal display panel

compare to Listerine® Total Care Anticavity Mouthwash active ingredient*

EQUALINE®

multiple benefit

anticavity mouthwash

sodium fluoride and acidulated phosphate topical solution

- helps strengthen teeth to help prevent cavities
- helps restore enamel
- kills germs that cause bad breath

IMPORTANT: read directions for proper use.

mint eucalyptus

33.8 FL OZ (1.05 QT) 1 L